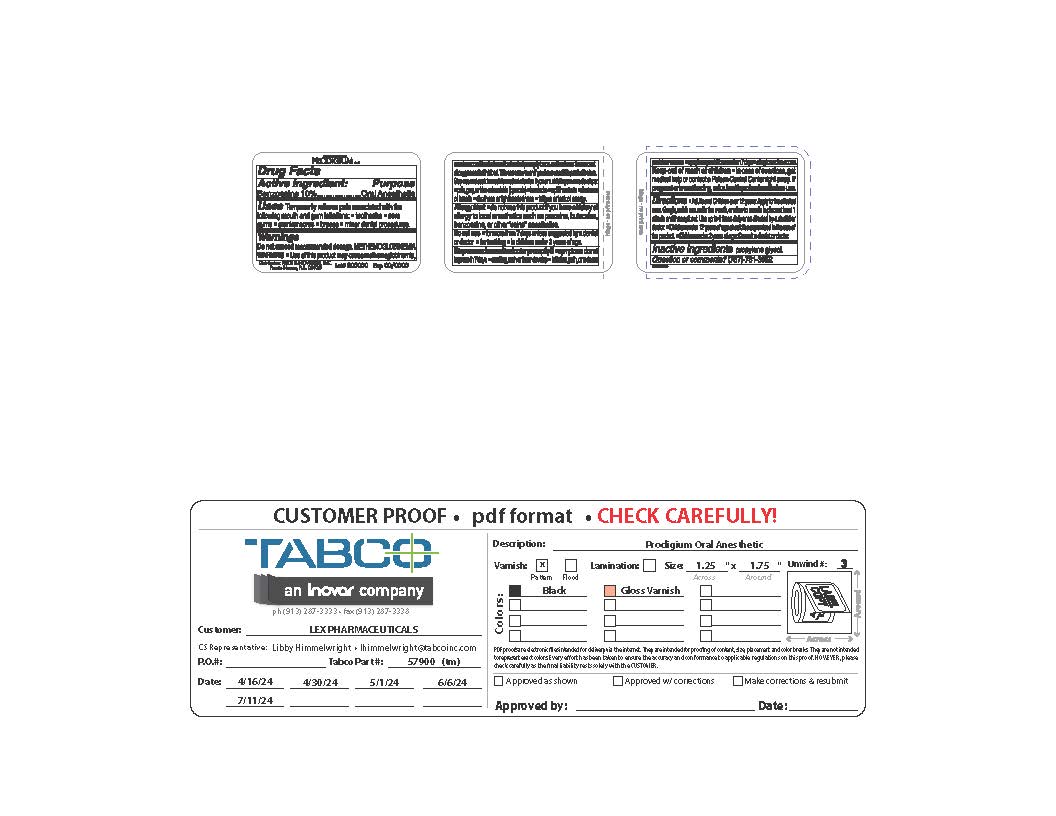 DRUG LABEL: Prodigium
NDC: 54361-7020 | Form: LIQUID
Manufacturer: Price & Novelties, Inc
Category: otc | Type: HUMAN OTC DRUG LABEL
Date: 20250108

ACTIVE INGREDIENTS: BENZOCAINE 10 mg/100 mL
INACTIVE INGREDIENTS: PROPYLENE GLYCOL

Prodigium

Active Ingredients: (%) Purpose

Benzocaine USP 10%..................Oral Anesthetic

Purpose

Oral Anesthetic

Uses

For temporary relief of pain associated with the following mouth and gum irritations:

- toothache
- sore gums
- cranker sores
- braces
- minor dental procedures

Warnings

Do not exceed recommended dosage

Methemoglobinemia warning: Use of this product may cause methemoglobinemia, a serious condition that must be treated promptly because it reduces the amount of oxygen carried in the blood. This can occur even if you have used this product before. Stop use and seek immediate medical attention if you or a child in your care develops:

- pale, gray, or blue colored skin (cyanosis)
- headache
- rapid heart rate
- shortness of breath
- dizziness or lightheadedness
- fatigue or lack of energy

Allergy alert

- do not use this product if you have a history of allergy to local anesthetics such as procaine, butacaine, benzocaine, or other "caine" anesthetics.

Do not use:

- for more than 7 days unless directed by a dentist or doctor.
- For teething
- in children under 2 years of age

Keep out of reach of children. In case of overdose, get medical help or contact a Poison Control Center right away. If pregnant or breastfeeding, ask a health professional before use.

Directions

•adults and children over 12 years of age apply to the affected area. Gargle, swish around the mouth or allow to remain in place at least 1 minute and then spit out. Use up to 4 times daily or as directed by a dentist or doctor. •children under 12 years of age should be supervised in the use of the product • Children under 2 years of age: Consult a dentist or doctor

Inactive Ingredients:

polyethylene glycol

Questions or comments?

787-781-3352

Stop use and consult a doctor promptly if:

- symptoms do not improve in 7 days
- swelling, rash, or fever develop
- irritation, pain, or redness persist or worsen
- symptoms persist for more than 7 days
- allergic reaction occurs